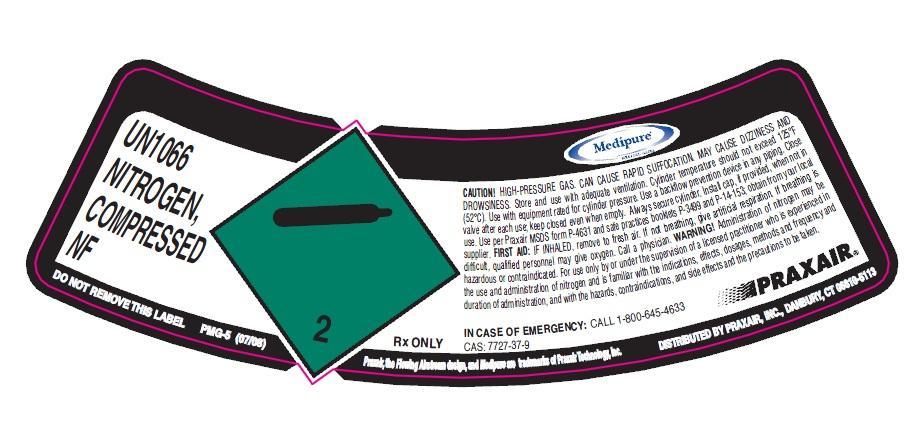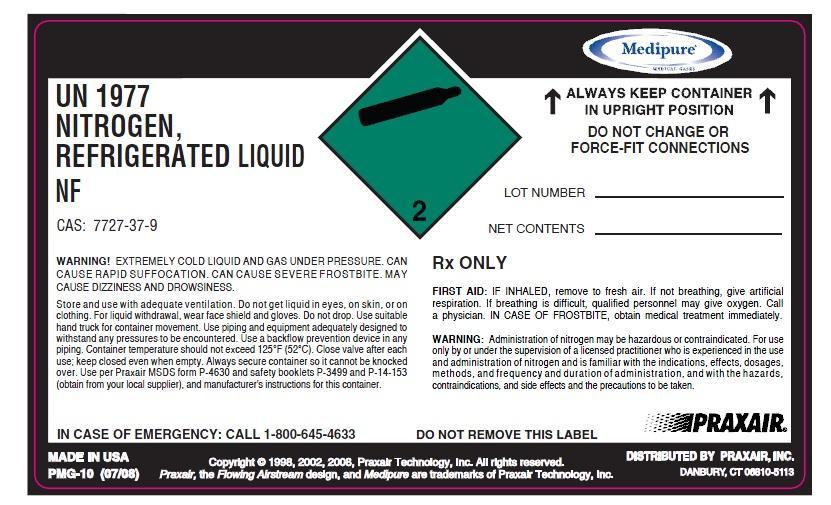 DRUG LABEL: Nitrogen
NDC: 15408-002 | Form: GAS
Manufacturer: Westair Gas & Equipment, LLC
Category: prescription | Type: HUMAN PRESCRIPTION DRUG LABEL
Date: 20130723

ACTIVE INGREDIENTS: Nitrogen 990 mL/1 L

Nitrogen

PACKAGE LABEL

UN166 NITROGEN, COMPRESSED NF
CONTENTS LOT NUMBER
CAUTION! HIGH-PRESSURE GAS. CAN CAUSE RAPID SUFFOCATION. MAY CAUSE DIZZINESS AND
(52°C). Use with equipment rated for cylinder pressure. Use a backflow prevention device in any piping. Close
valve after each use; keep closed even when empty. Always secure cylinder. Install cap, if provided, when not in use. Use per Praxair MSDS form P-4631 and safe practices booklets P-3499 and P-14-153; obtain from your local supplier. FIRST AID: IF INHALED, remove to fresh air. If not breathing, give artificial respiration. If breathing is
difficult, qualified personnel may give oxygen. Call a physician. WARNING! Administration of nitrogen may be
hazardous or contraindicated. For use only by or under the supervision of a licensed practitioner who is experienced in the use and administration of nitrogen and is familiar with the indications, effects, dosages, methods and frequency and duration of administration, and with the hazards, contraindications, and side effects and the precautions to be taken.
Rx ONLY CAS 7727-37-8
IN CASE OF EMERGENCY: CALL 1-800-645-4633
DISTRIBUTED BY PRAXAIR, INC., DANBURY
DO NOT REMOVE THIS LABEL PMG-4 (11/07)
Copyright @ 2002, 2005, 2007, Praxair Technology, inc.
Praxair, the flowing airstream design and Medipure are trademarks of Praxair Technology, Inc. DISTRIBUTED BY PRAXAIR, INC, DANBURY, CT 06810-5113

PACKAGE LABEL

UN1977 NITROGEN, REFRIGERATED LIQUID NF
ALWAYS KEEP CONTINER IN UPRIGHT POSITION. DO NOT CHANGE OR FORCE-FIT CONNECTIONS
LOT #
NET CONTENTS
WARNING! EXTREMELY COLD LIQUID AND GAS UNDER PRESSURE. CAN CAUSE RAPID SUFFOCATION. CAN CAUSE SEVERE FROSTBITE. MAY CAUSE DIZZINESS AND DROWSINESS.
Store and use with adequate ventilation. Do not get liquid in eyes, on skin, or on clothing. For liquid withdrawal, wear face shield and gloves. Do not drop. Use suitable hand truck for container movement. Use piping and equipment adequately designed to
withstand any pressures to be encountered. Use a backflow prevention device in any piping. Container temperature should not exceed 125°F (52°C). Close valve after each use; keep closed even when empty. Always secure container so it cannot be knocked over. Use per Praxair MSDS form P-4630 and safety booklets P-3499 and P-14-153 (obtain from your local supplier), and manufacturer's instructions for this container
RX ONLY
FIRST AID: IF INHALED, remove to fresh air. If not breathing, give artificial respiration. If breathing is difficult, qualified personnel may give oxygen. Call a physician. IN CASE OF FROSTBITE, obtain medical treatment immediately.
WARNING: Administration of nitrogen may be hazardous or contraindicated. For use only by or under the supervision of a licensed practitioner who is experienced in the use and Administration of nitrogen and is familiar with the indications, effects, dosages, methods, and frequency and duration of administration, and with the hazards, contraindications, and side effects and the precautions to be taken.
DO NOT REMOVE THIS LABEL
Rx ONLY CAS 7727-37-9 PRODUCED BY AIR LIQUEFACTION
IN CASE OF EMERGENCY: CALL 1-800-645-4633
DISTRIBUTED BY PRAXAIR, INC., DANBURY
PMG-10 (07/08)
Copyright @ 1998, 2002, 2008. Praxair Technology, Inc. All rights reserved
Praxair, the flowing airstream design and Medipure are trademarks of Praxair Technology, Inc. DISTRIBUTED BY PRAXAIR, INC, DANBURY, CT 06810-5113